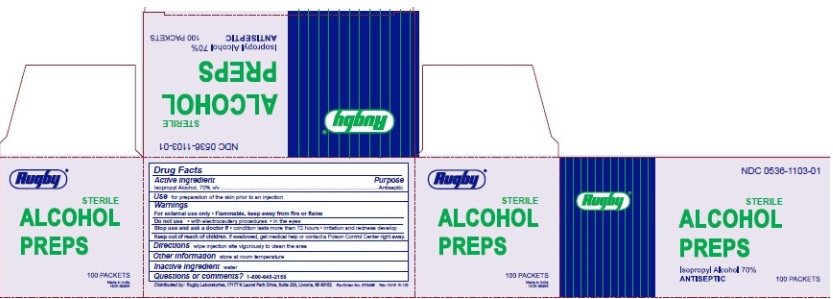 DRUG LABEL: Alcohol Prep Pad
NDC: 0536-1103 | Form: SWAB
Manufacturer: Rugby Laboratories
Category: otc | Type: HUMAN OTC DRUG LABEL
Date: 20251023

ACTIVE INGREDIENTS: ISOPROPYL ALCOHOL 0.7 mL/1 mL
INACTIVE INGREDIENTS: WATER

Rugby Alcohol Prep Pads

Active ingredient

Active Ingredients

Isopropyl Alcohol 70% v/v

Purpose

Antiseptic

Use

For preparation of the skin prior to an injection

Warnings

- For External Use Only
- Flammable, Keep away from fire or flame

Do not use

- with electrocautery procedures
- In the Eyes.

Stop Use and ask a Doctor if

•condition lasts more than 72 hours•irritation and redness develop

Keep out of reach of children

If swallowed, get medical help or contact a Poison Control Center right away.

Directions

Wipe injection site vigorously to clean the area

Other Information

Store at Room Temperature

Inactive ingredient

water

Questions or comments?

1-800-645-2158

Made in India

Distributed by:

Rugby Laboratories

17177 N Laurel Park Drive, Suite 233

Livonia, MI 48152

Principal Display Panel

NDC0536-1103-01

Rugby

Sterile Alcohol Preps

Isopropyl Alcohol 70%

100 Packets

Reorder No. 370458